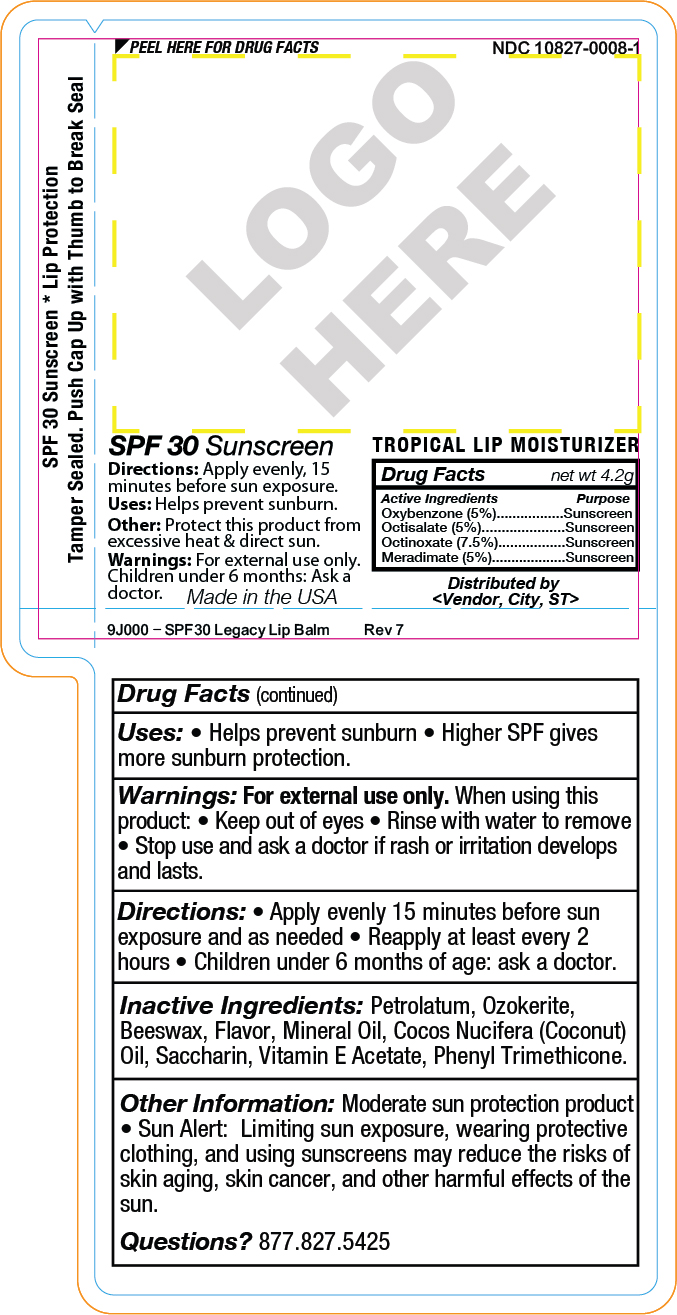 DRUG LABEL: YMLABS
NDC: 10827-0008 | Form: STICK
Manufacturer: Yusef Manufacturing Laboratories
Category: otc | Type: HUMAN OTC DRUG LABEL
Date: 20220125

ACTIVE INGREDIENTS: MERADIMATE 0.21 g/4.2 g; OCTINOXATE 0.315 g/4.2 g; OCTISALATE 0.21 g/4.2 g; OXYBENZONE 0.21 g/4.2 g
INACTIVE INGREDIENTS: PETROLATUM; CERESIN; WHITE WAX; MINERAL OIL; COCONUT OIL; SACCHARIN; ALPHA-TOCOPHEROL ACETATE; PHENYL TRIMETHICONE

YMlabs SPF30 Flavored Lip Balm

SPF 30 Sunscreen

Uses: Helps prevent sunburn.
Directions: Apply evenly, 15
minutes before sun exposure.
Other: Protect this product from
excessive heat & direct sun.
Warnings: For external use only.
Children under 6 months: Ask a
doctor.

Drug Facts net wt 4.2g
Active Ingredients Purpose

Meradimate (5%)...........Sunscreen

Octinoxate (7.5%).............Sunscreen

Octisalate (5%)..............Sunscreen
Oxybenzone (5%)...........Sunscreen

Made in the USA

Distributed by
<Vendor, City, ST>

Drug Facts (continued)
Uses: • Helps prevent sunburn • Higher SPF gives
more sunburn protection.

Warnings: For external use only. When using this
product: • Keep out of eyes • Rinse with water to remove
• Stop use and ask a doctor if rash or irritation develops
and lasts.

INSTRUCTIONS FOR USE

Directions: • Apply evenly 15 minutes before sun
exposure and as needed • Reapply at least every 2
hours • Children under 6 months of age: ask a doctor.

Inactive Ingredients: Petrolatum, Ozokerite,
Beeswax, Mineral Oil, Coconut Oil, Flavor, Saccharin,
Phenyl Trimethicone, Safflower Seed Oil, Aloe Oil,
Vitamin E Acetate

Other Information: Moderate sun protection product
• Sun Alert: Limiting sun exposure, wearing protective
clothing, and using sunscreens may reduce the risks of
skin aging, skin cancer, and other harmful effects of the
sun.
Questions? 877.827.5425